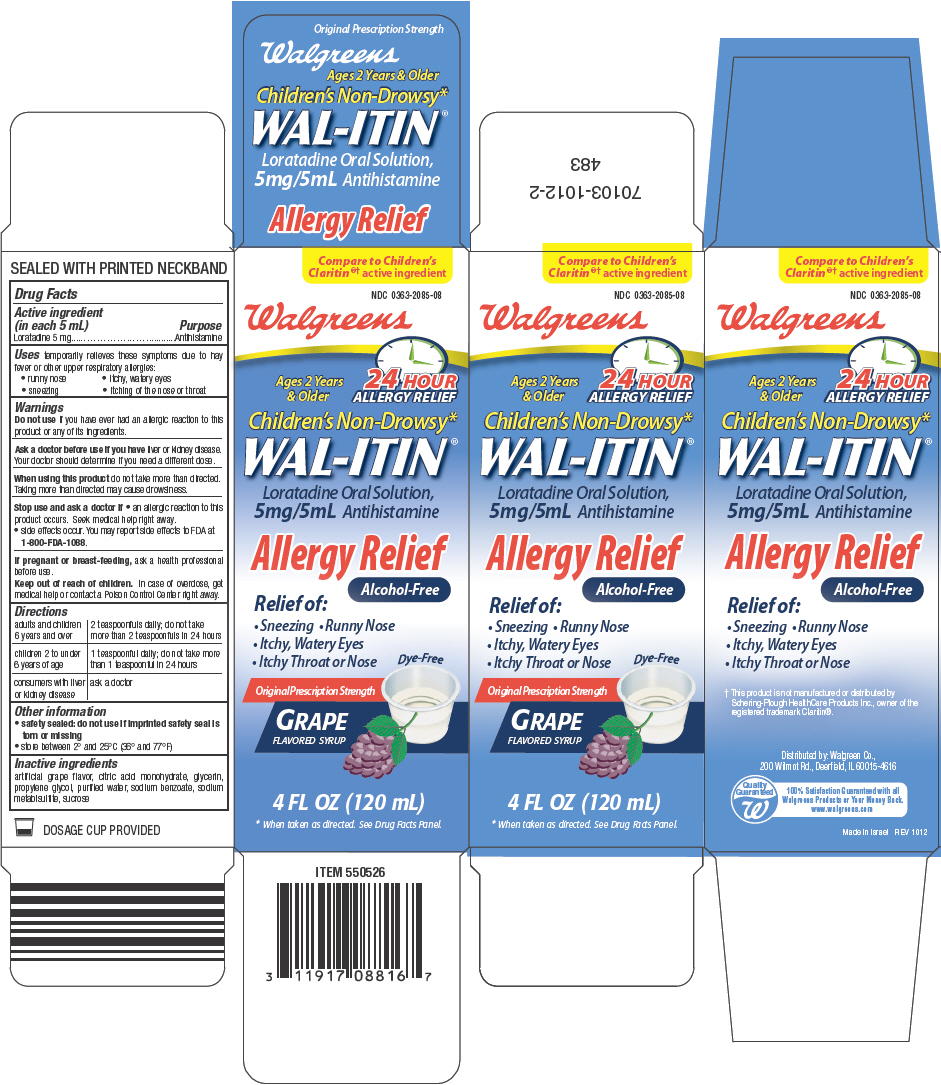 DRUG LABEL: Wal-itin Allergy Relief
NDC: 0363-2085 | Form: SOLUTION
Manufacturer: Walgreen Company
Category: otc | Type: HUMAN OTC DRUG LABEL
Date: 20130122

ACTIVE INGREDIENTS: Loratadine 5 mg/5 mL
INACTIVE INGREDIENTS: citric acid monohydrate; glycerin; propylene glycol; water; sodium benzoate; sodium metabisulfite; sucrose

Wal-itin® Allergy Relief

Drug Facts

Active ingredient (in each 5 mL)

Loratadine 5 mg

Purpose

Antihistamine

Uses

temporarily relieves these symptoms due to hay fever or other upper respiratory allergies:

- runny nose
- itchy, watery eyes
- sneezing
- itching of the nose or throat

Warnings

Do not use if you have ever had an allergic reaction to this product or any of its ingredients.

Ask a doctor before use if you have liver or kidney disease. Your doctor should determine if you need a different dose.

When using this product do not take more than directed. Taking more than directed may cause drowsiness.

Stop use and ask a doctor if

- an allergic reaction to this product occurs. Seek medical help right away.
- side effects occur. You may report side effects to FDA at 1-800-FDA-1088.

PREGNANCY OR BREAST FEEDING

If pregnant or breast-feeding, ask a health professional before use.

Keep out of reach of children. In case of overdose, get medical help or contact a Poison Control Center right away.

Directions

adults and children 6 years and over | 2 teaspoonfuls daily; do not take more than 2 teaspoonfuls in 24 hours
children 2 to under 6 years of age | 1 teaspoonful daily; do not take more than 1 teaspoonful in 24 hours
consumers with liver or kidney disease | ask a doctor

Other information

- safety sealed: do not use if imprinted safety seal is torn or missing
- store between 2° and 25°C (36° and 77°F)

Inactive ingredients

artificial grape flavor, citric acid monohydrate, glycerin, propylene glycol, purified water, sodium benzoate, sodium metabisulfite, sucrose

Distributed by: Walgreen Co.,
200 Wilmot Rd., Deerfield, IL 60015-4616

PRINCIPAL DISPLAY PANEL - 120 mL Bottle Carton

Compare to Children's
Claritin†® active ingredient

NDC 0363-2085-08

Walgreens

Ages 2 Years
& Older

24 HOUR
ALLERGY RELIEF

Children's Non-Drowsy*
WAL-ITIN®

Loratadine Oral Solution,
5mg/5mL Antihistamine

Allergy Relief
Alcohol-Free

Relief of:

- Sneezing • Runny Nose
- Itchy, Watery Eyes
- Itchy Throat or Nose

Dye-Free

Original Prescription Strength

GRAPE
FLAVORED SYRUP

4 FL OZ (120 mL)

* When taken as directed. See Drug Facts Panel.